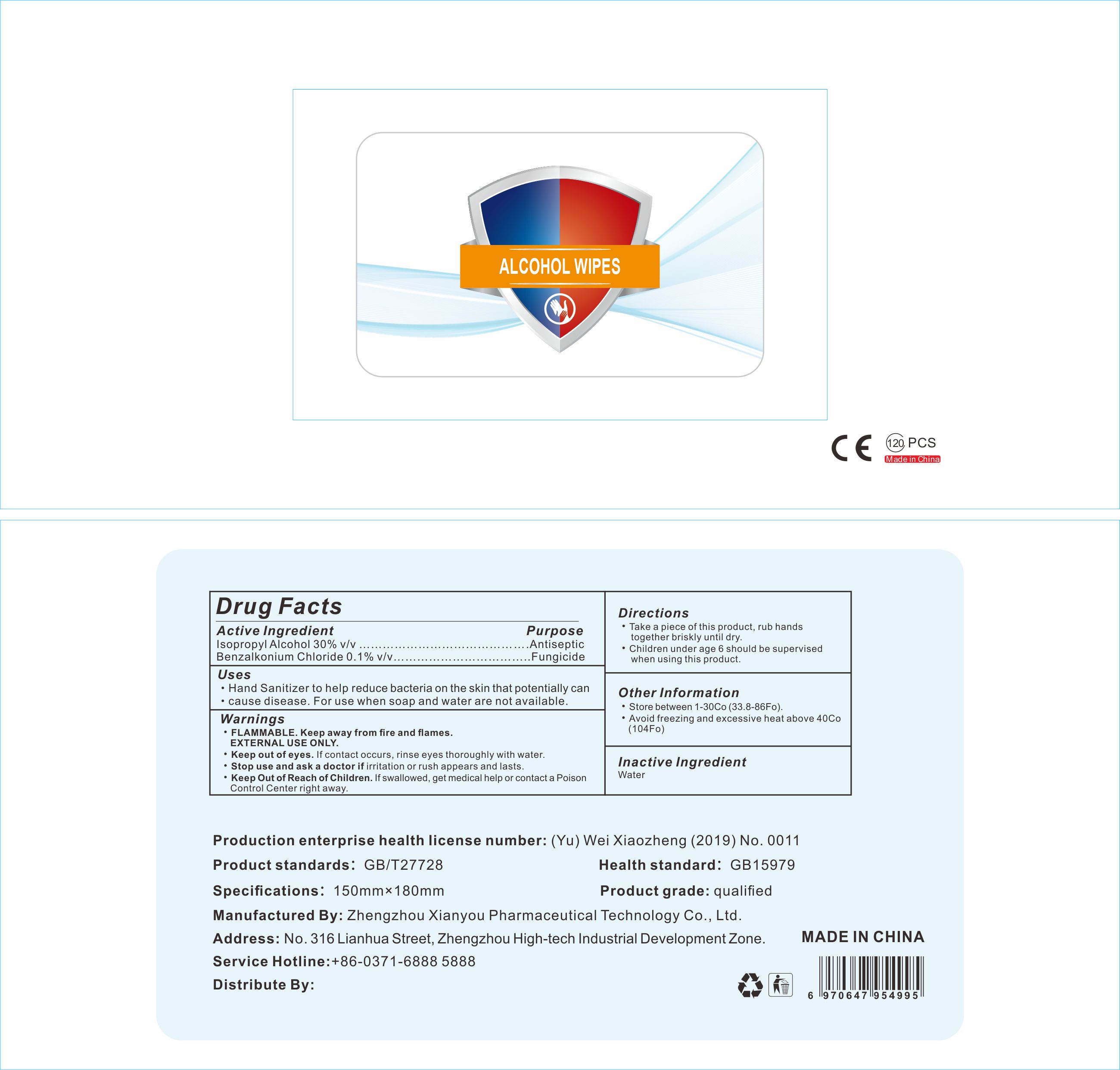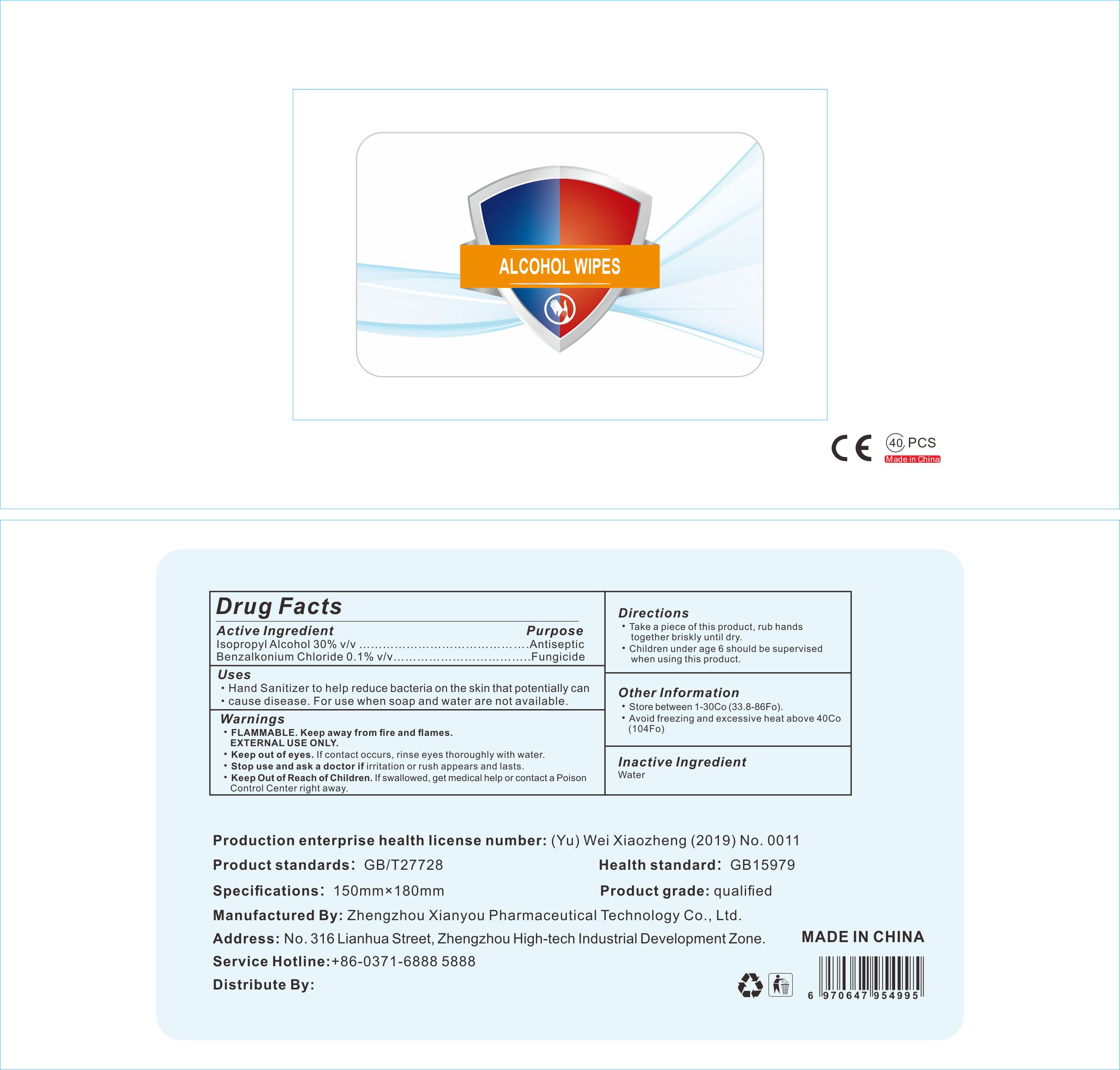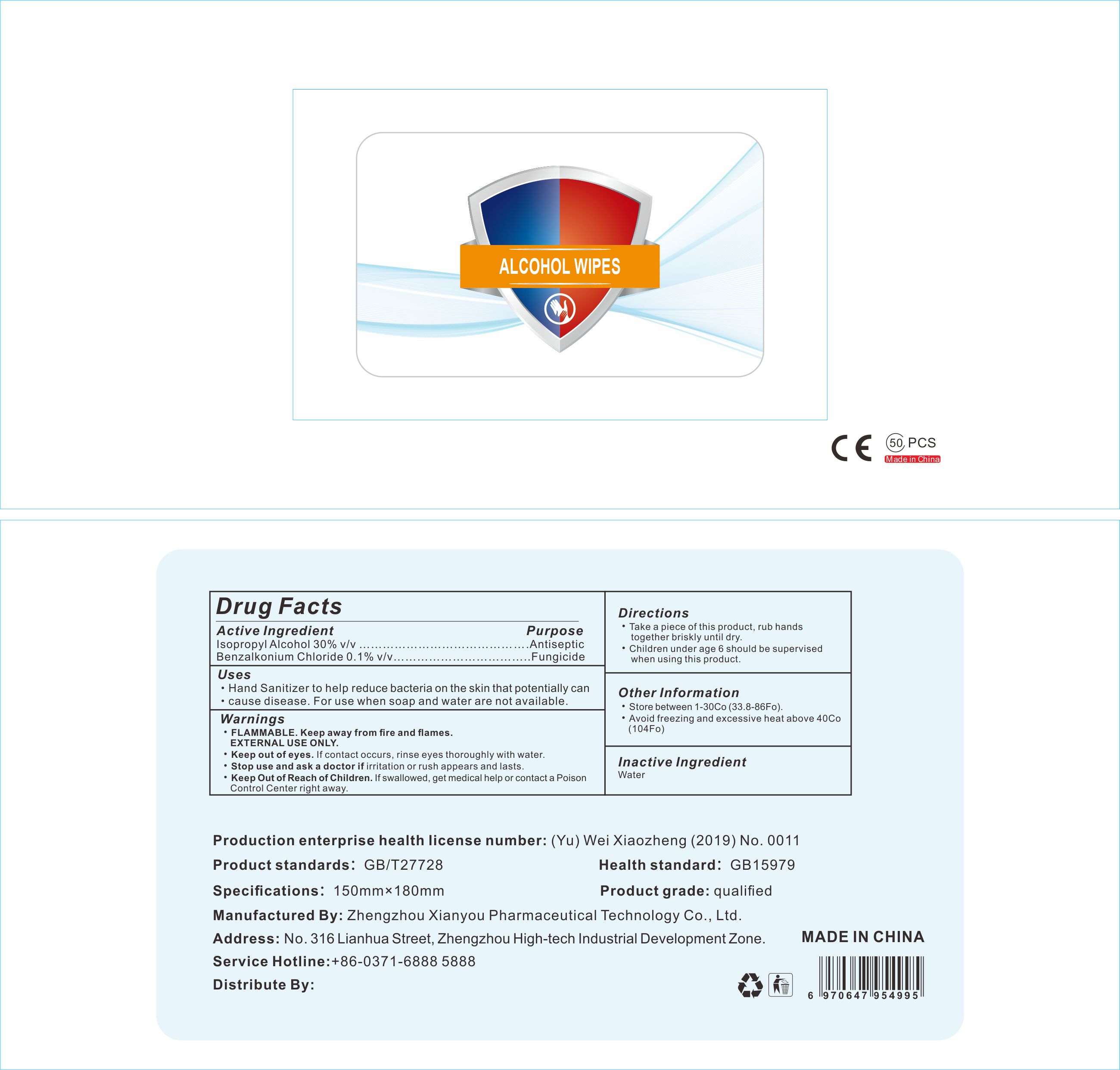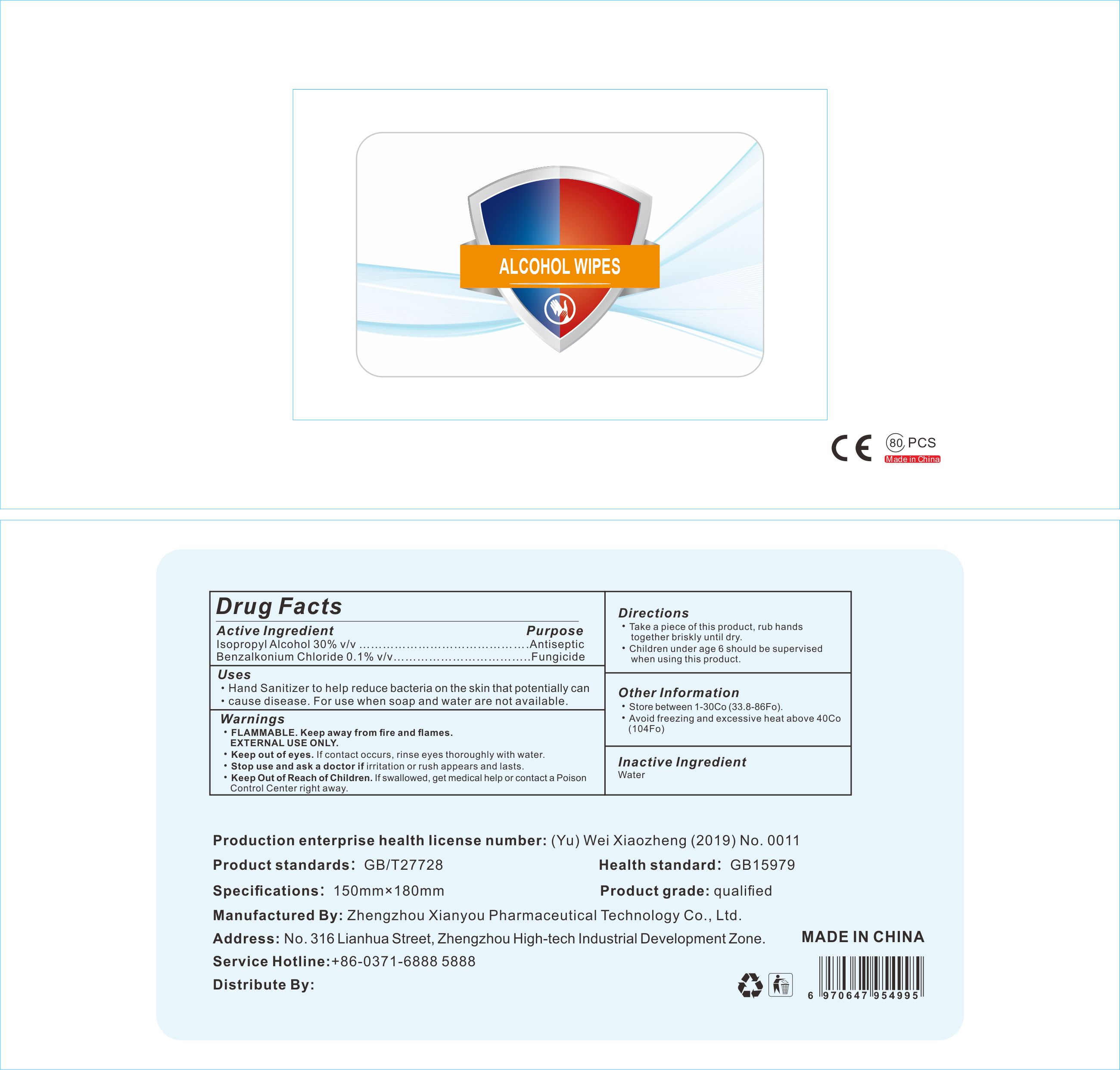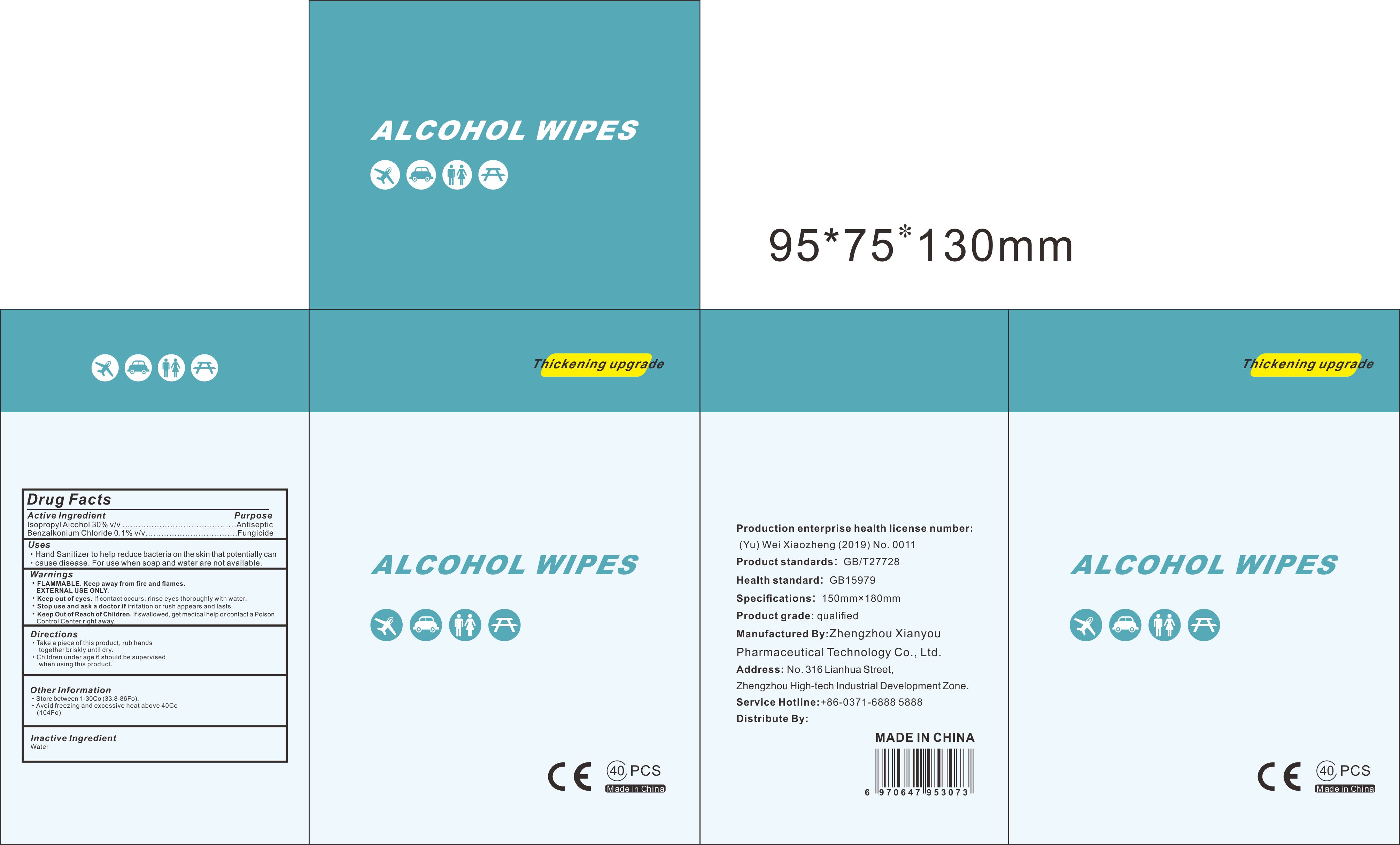 DRUG LABEL: Xianyou Hand Sanitizer Alcohol Wipes
NDC: 79001-001 | Form: CLOTH
Manufacturer: Zhengzhou Xianyou Pharmaceutical Technology Co., Ltd.
Category: otc | Type: HUMAN OTC DRUG LABEL
Date: 20200702

ACTIVE INGREDIENTS: ISOPROPYL ALCOHOL 0.669 U/100 mL; BENZALKONIUM CHLORIDE 0.001 mg/100 mL
INACTIVE INGREDIENTS: WATER 0.3 U/100 mL

Xianyou Hand Sanitizer Alcohol Wipes

This is a hand sanitizer Alcohol wipes manufactured according to the Temporary Policy for Preparation of Certain Alcohol-Based Hand Sanitizer Products During the Public Health Emergency (CoViD-19); Guidance for Industry.

The hand sanitizer is manufactured using only the following United States Pharmacopoeia (USP) grade ingredients in the preparation of the product (percentage in final product formulation) consistent with World Health Organization (WHO) recommendations:

1. Isopropyl Alcohol (75%, v/v) in an aqueous solution denatured according to Alcohol and Tobacco Tax and Trade Bureau regulations in 27 CFR part 20.
2. Benzalkonium Chloride (0.1% v/v).
3. Water

The firm does not add other active or inactive ingredients. Different or additional ingredients may impact the quality and potency of the product.

Active Ingredient(s)

Isopropyl Alcohol 75% v/v. Purpose: Antiseptic

Benzalkonium Chloride 0.1% v/v. Purpose:Fungicide

Purpose

Antiseptic, Hand Sanitizer

Use

Hand Sanitizer to help reduce bacteria that potentially can cause disease. For use when soap and water are not available. Not Recommended for repeated use.

Warnings

For external use only. Flammable. Keep away from heat or flame

Do not use

- in children less than 2 months of age
- on open skin wounds

When using this product keep out of eyes, ears, and mouth. In case of contact with eyes, rinse eyes thoroughly with water.
Stop use and ask a doctor if irritation or rash occurs. These may be signs of a serious condition.
Keep out of reach of children. If swallowed, get medical help or contact a Poison Control Center right away.

Stop use and ask a doctor if irritation or rash occurs. These may be signs of a serious condition.

Keep out of reach of children. If swallowed, get medical help or contact a Poison Control Center right away.

Directions

- Take a piece of this product, rub hands together until dry.
- Supervise children under 6 years of age when using this product to avoid swallowing.

Other information

- Store between 15-30C (59-86F)
- Avoid freezing and excessive heat above 40C (104F)

Inactive ingredients

purified water

Package Label - Principal Display Panel

40 pcs NDC: 79001-001-40

50 pcs NDC: 79001-001-50 80 pcs NDC: 79001-001-80 120 pcs NDC: 79001-001-12 40 pcs NDC: 79001-001-41